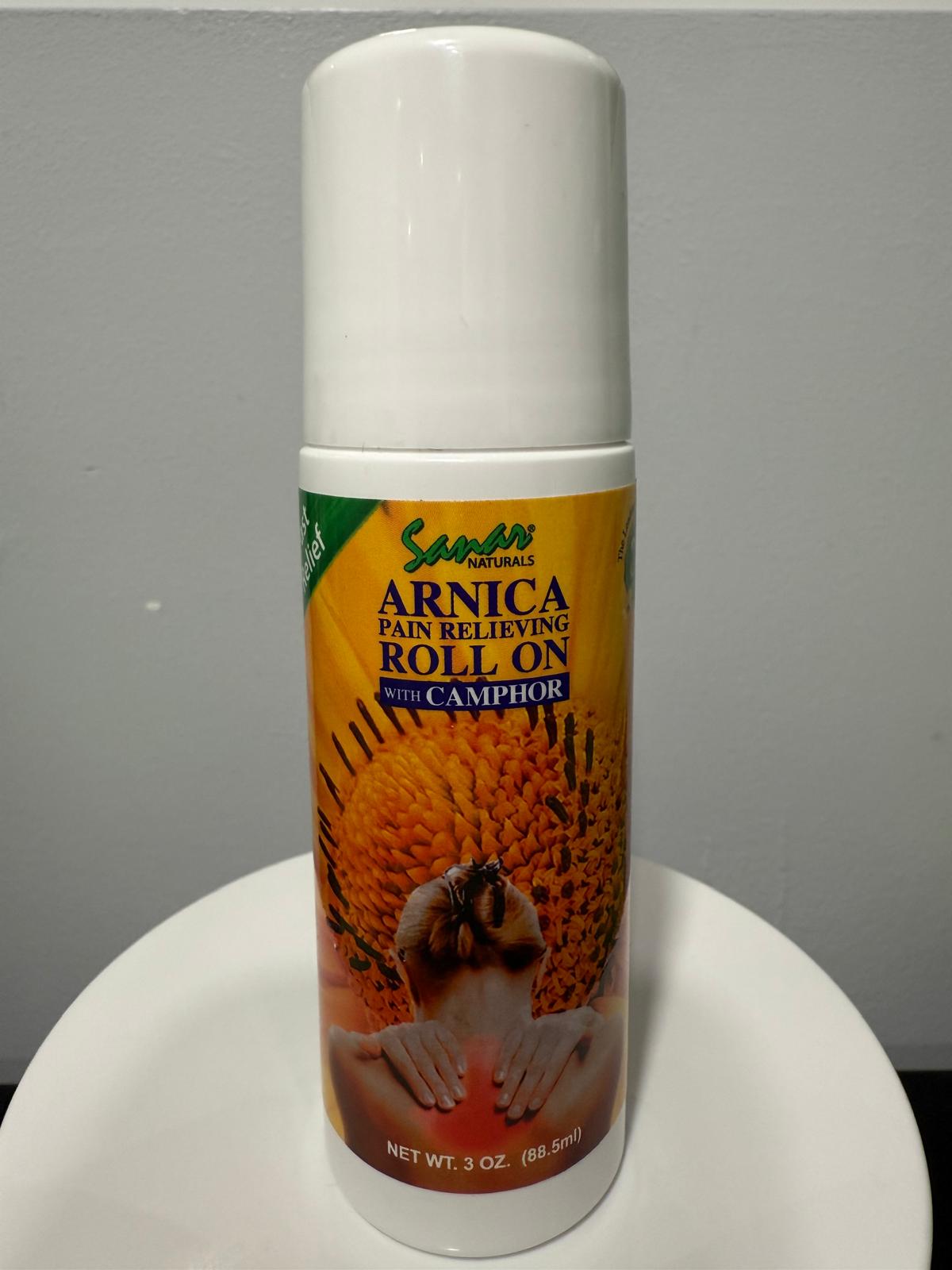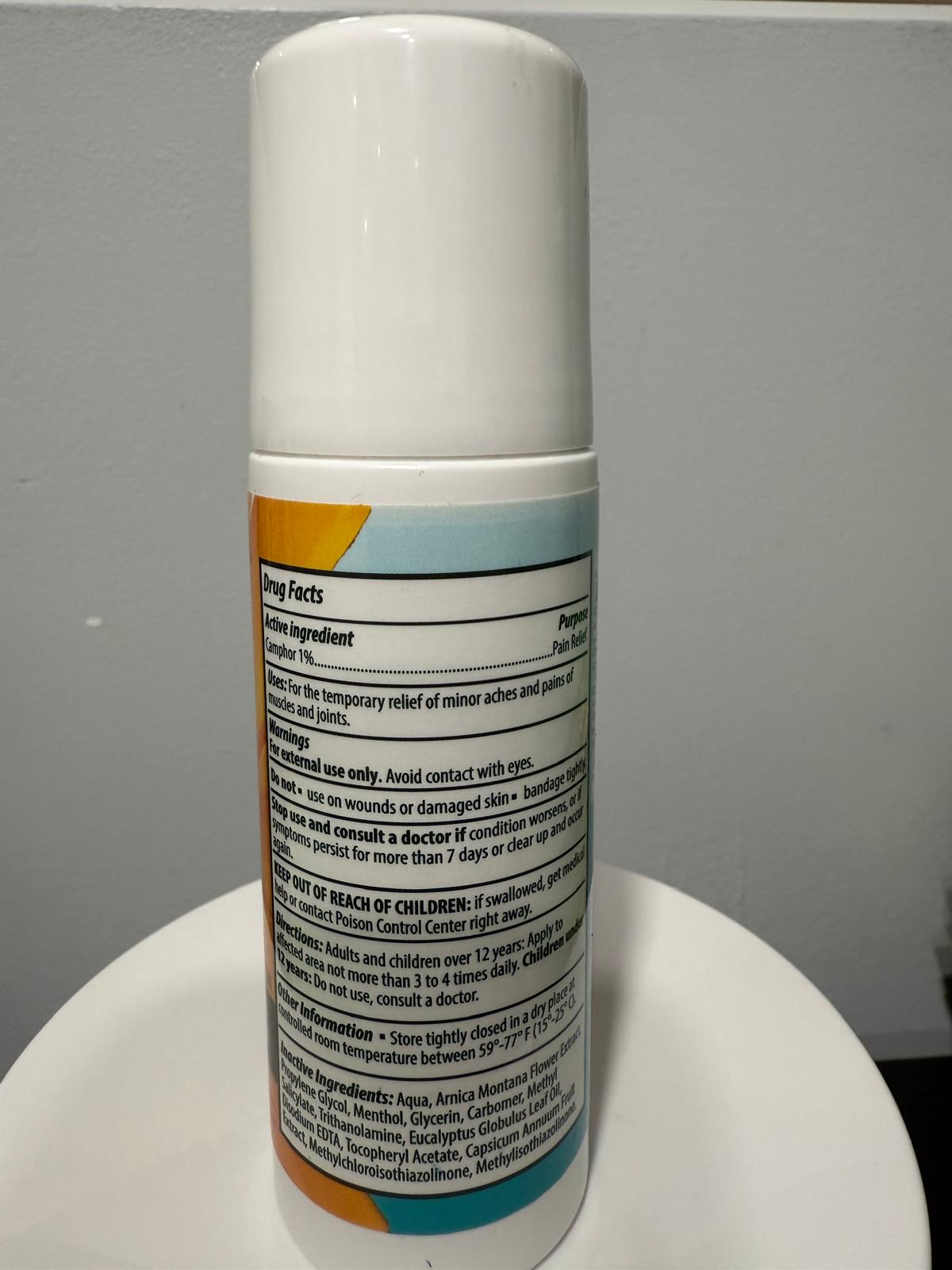 DRUG LABEL: SANAR NATURAL-ARNICA ROLL ON
NDC: 84178-010 | Form: CREAM
Manufacturer: EVI LABS
Category: otc | Type: HUMAN OTC DRUG LABEL
Date: 20250212

ACTIVE INGREDIENTS: CAMPHOR (SYNTHETIC) 0.885 g/88.5 g
INACTIVE INGREDIENTS: EUCALYPTUS GLOBULUS LEAF 0.885 g/88.5 g; METHYLISOTHIAZOLINONE 0.35 g/88.5 g; GLYCERIN 2.655 g/88.5 g; MINERAL OIL 1.77 g/88.5 g; PROPYLENE GLYCOL 0.885 g/88.5 g; .ALPHA.-TOCOPHEROL 0.044 g/88.5 g; CAPSICUM ANNUUM WHOLE 0.885 g/88.5 g; WATER 69.005 g/88.5 g; TRIETHANOLAMINE 0.03 g/88.5 g; CARBOMER 940 0.443 g/88.5 g; METHYLCHLOROISOTHIAZOLINONE 0.235 g/88.5 g; CETEARYL ALCOHOL 2.655 g/88.5 g; GLYCERYL MONOSTEARATE 0.885 g/88.5 g; ARNICA MONTANA FLOWER 1.77 g/88.5 g; MENTHOL 0.885 g/88.5 g; METHYL SALICYLATE 3.9825 g/88.5 g; EDETATE DISODIUM 0.177 g/88.5 g

Sanar Natural-ARNICA PAIN RELIEVING ROLL ON

Active Ingredient

Camphor 1%

Purpose

Pain Relief

Uses

For the temporary relief of minor aches and pains of muscles and joints.

Warnings

For external use only. Avoid contact with eyes

Warnings

- Do not use on wounds or damaged skin
- Do not bandage tightly

Stop use and cosult a doctor if condition worsens, or if symptoms persist for more than 7 days or dear up and occur again.

Keep out of reach of children: if swallowed, get medical help or contact Poison Control Center right away.

Directions

Directions: Adults and Children over 12 years Apply to affected area not more than 3 or 4 times daily. Childen under 12 years Do not use, consult a Doctor.

Other Information

Store tightly dosed in a dry place at a controlled room temperature between 59º- 77ºF (15º-25ºC).

Inactive Ingredient

Inactive Ingredient: Aqua, Arnica Montana Flower Extract, Propylene Glycol, Menthol, Glycerin, Carbomer, Methyl Salicylate, Triethanolamine, Eucalyptus Globulus Leaf Oil, Disodium EDTA, Tocopheryl Acetate, Capsicum Ammum Fruit Extract, Methylchloroisothiazolinone, Methylisothiazolinone.

Dosage & Administration

Apply to the affected area not more than 3 or 4 times daily.

Drug Facts

Principal Display Panel: Drug Facts.